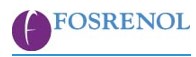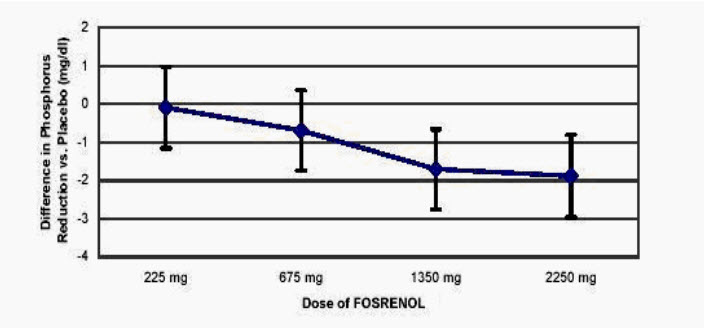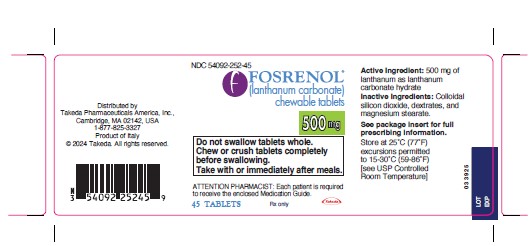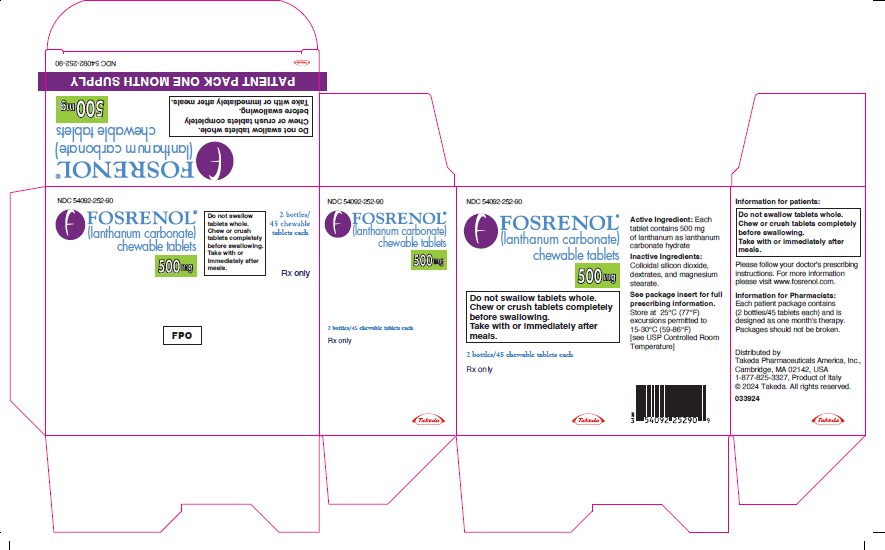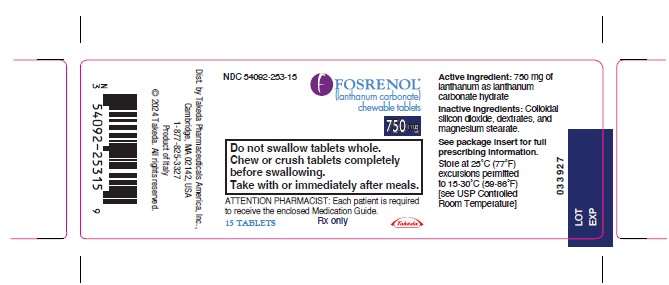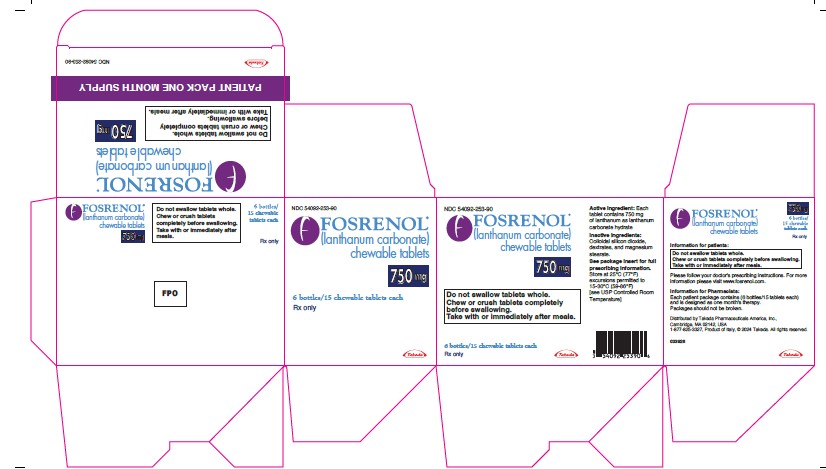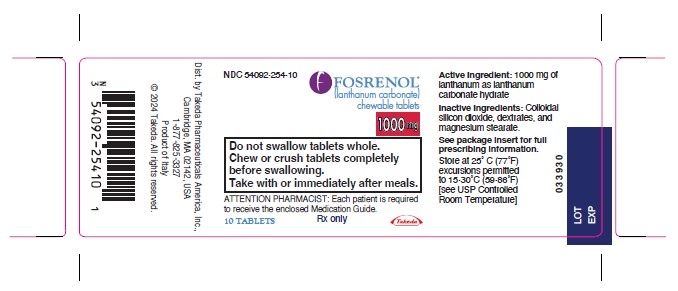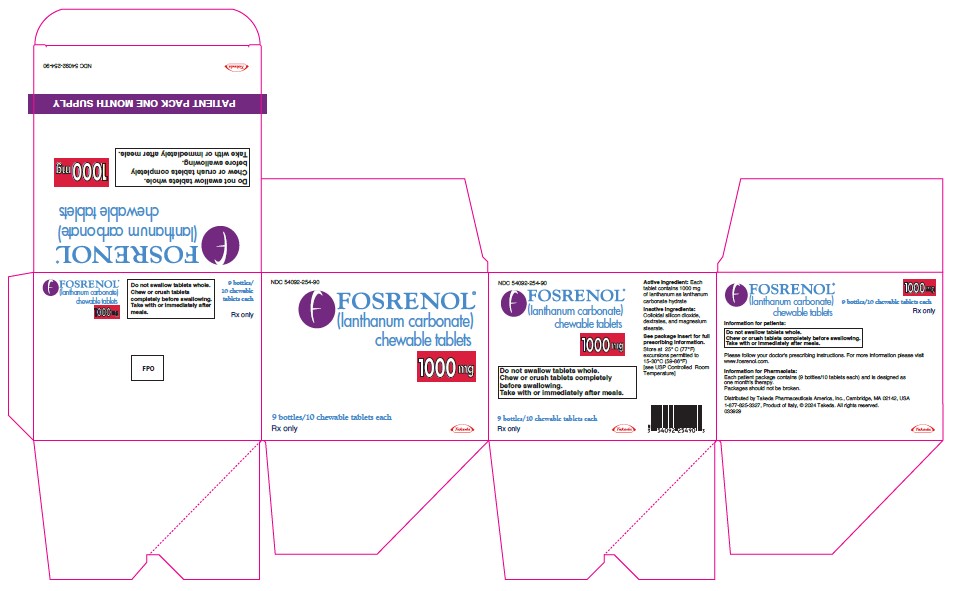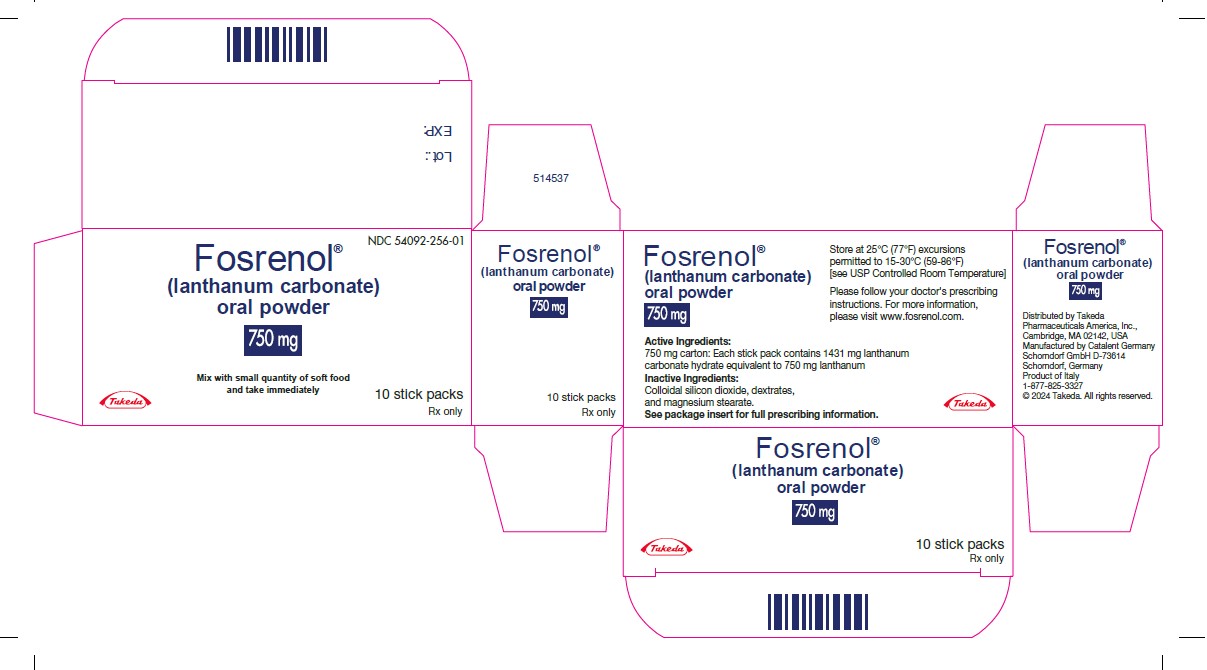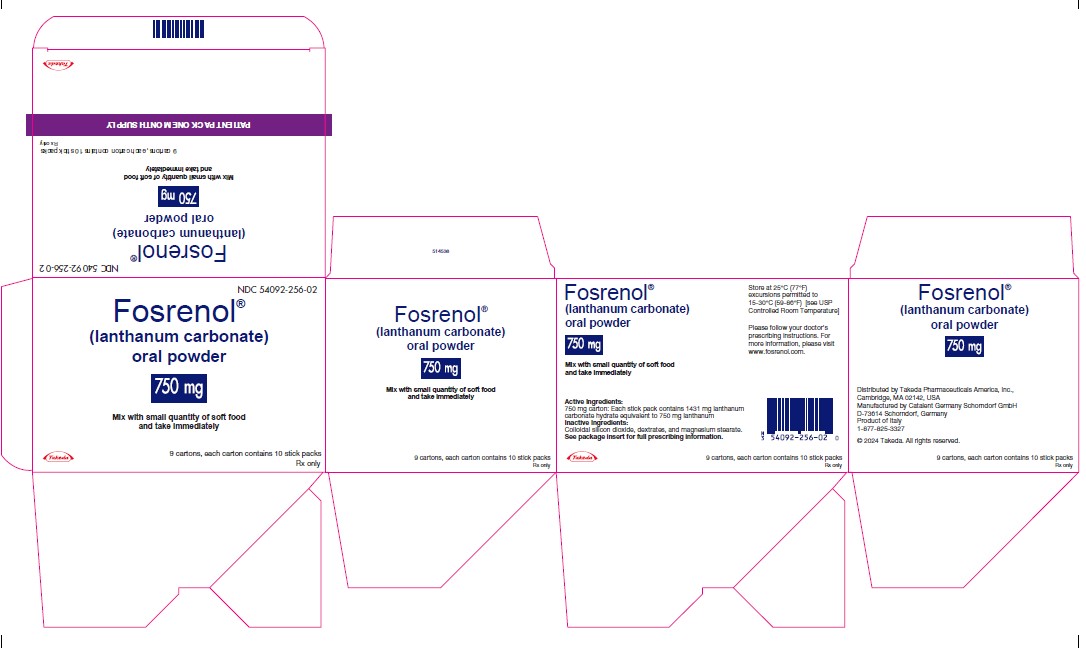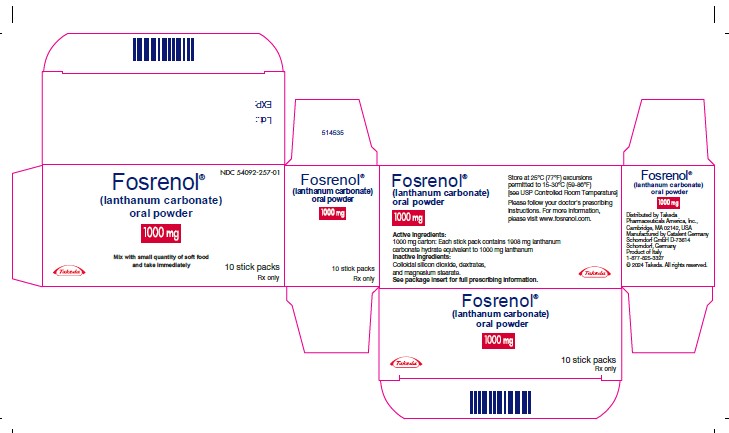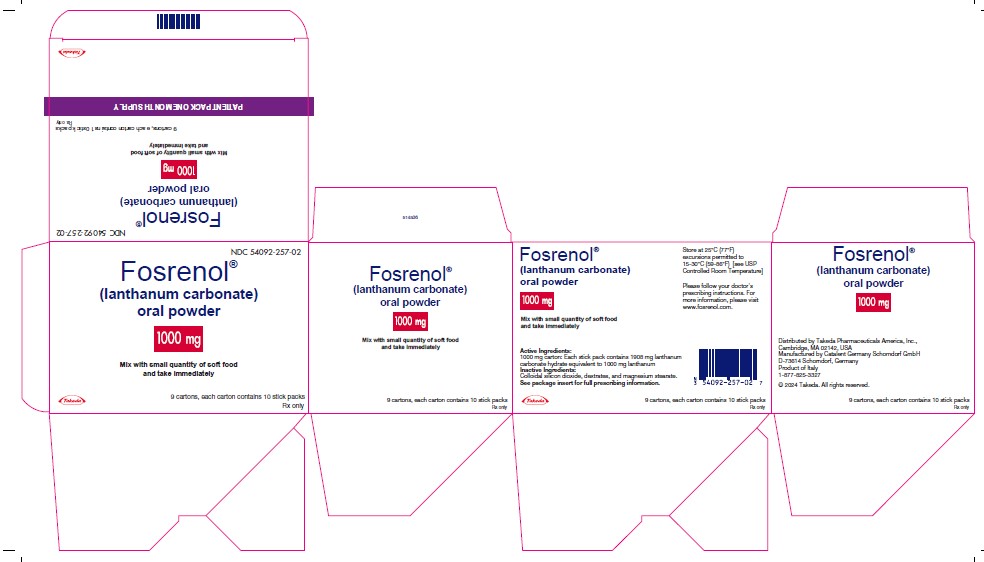 DRUG LABEL: Fosrenol
NDC: 54092-252 | Form: TABLET, CHEWABLE
Manufacturer: Takeda Pharmaceuticals America, Inc.
Category: prescription | Type: HUMAN PRESCRIPTION DRUG LABEL
Date: 20241231

ACTIVE INGREDIENTS: LANTHANUM CARBONATE 500 mg/1 1
INACTIVE INGREDIENTS: DEXTRATES; SILICON DIOXIDE; MAGNESIUM STEARATE

HIGHLIGHTS OF PRESCRIBING INFORMATION

These highlights do not include all the information needed to use FOSRENOL safely and effectively. See full prescribing information for FOSRENOL.
FOSRENOL® (lanthanum carbonate) chewable tablets, for oral use
FOSRENOL® (lanthanum carbonate) oral powder, for oral use
Initial U.S. Approval: 2004

RECENT MAJOR CHANGES

Contraindications (4) | 08/2024
Warnings and Precautions (5.2) | 12/2023

1 INDICATIONS AND USAGE

- FOSRENOL is a phosphate binder indicated to reduce serum phosphate in patients with end-stage renal disease (ESRD). (1)

2 DOSAGE AND ADMINISTRATION

- The recommended initial total daily dose of FOSRENOL is 1,500 mg in divided doses. Titrate every 2 to 3 weeks based on serum phosphate level. (2)
- Take FOSRENOL with or immediately after meals. (2)
- FOSRENOL Chewable Tablets: Chew or crush tablet completely before swallowing. (2)
- FOSRENOL Oral Powder: Sprinkle powder on a small quantity of applesauce or other similar food and consume immediately. Consider powder formulation in patients with poor dentition or who have difficulty chewing tablets. (2)

3 DOSAGE FORMS AND STRENGTHS

- FOSRENOL Chewable Tablets: 500 mg, 750 mg, and 1,000 mg. (3)
- FOSRENOL Oral Powder: 750 mg and 1,000 mg. (3)

4 CONTRAINDICATIONS

- Hypersensitivity to FOSRENOL or to any ingredient in the formulation. (4)
- Bowel obstruction, ileus, and fecal impaction. (4)

5 WARNINGS AND PRECAUTIONS

- Serious cases of gastrointestinal obstruction, ileus, subileus, gastrointestinal perforation, and fecal impaction. Risks include altered gastrointestinal anatomy, hypomotility disorders, and concomitant medications. Advise patients to chew or crush the tablet completely. (5.1)
- FOSRENOL has radio-opaque properties and, therefore, may give the appearance typical of an imaging agent during abdominal X-ray procedures. (5.2)

6 ADVERSE REACTIONS

- In controlled trials, the most common adverse reactions that were more frequent (≥5% difference vs. placebo) in FOSRENOL were nausea, vomiting, and abdominal pain. (6.1)
- The following adverse reactions have been identified during post-approval use of FOSRENOL: constipation, dyspepsia, allergic skin reactions, and tooth injury while chewing the tablet. (6.2)

To report SUSPECTED ADVERSE REACTIONS, contact Takeda Pharmaceuticals U.S.A., Inc. at 1-877-TAKEDA-7 (1-877-825-3327) or FDA at 1-800-FDA-1088 or www.fda.gov/medwatch.

7 DRUG INTERACTIONS

- There is a potential for FOSRENOL to interact with compounds that bind to cationic antacids (i.e., aluminum-, magnesium-, or calcium-based); therefore, do not take such compounds within 2 hours of dosing with FOSRENOL. (7.1)
- Oral quinolone antibiotics must be taken at least 1 hour before or 4 hours after FOSRENOL. (7.2)
- Do not take thyroid hormone replacement therapy within 2 hours of dosing with FOSRENOL. Monitoring of TSH levels is recommended in patients receiving both medicinal agents. (7.3)
- For oral medications where a reduction in the bioavailability of that medication would have a clinically significant effect on its safety or efficacy, consider separation of the timing of the administration of the two drugs. (7.4)

FULL PRESCRIBING INFORMATION

1 INDICATIONS AND USAGE

FOSRENOL® is a phosphate binder indicated to reduce serum phosphate in patients with end-stage renal disease (ESRD).

Management of elevated serum phosphorus levels in patients with ESRD usually includes all of the following: reduction in dietary intake of phosphate, removal of phosphate by dialysis, and reduction of intestinal phosphate absorption with phosphate binders.

2 DOSAGE AND ADMINISTRATION

Divide the total daily dose of FOSRENOL and take with or immediately after meals. The recommended initial total daily dose of FOSRENOL is 1,500 mg. Titrate the dose every 2 to 3 weeks until an acceptable serum phosphate level is reached. Monitor serum phosphate levels as needed during dose titration and on a regular basis thereafter.

FOSRENOL has the potential to bind other orally administered drugs; consider separating the administration of other oral medications [see Drug Interactions (7)].

In clinical studies of patients with ESRD, FOSRENOL doses up to 4,500 mg were evaluated. Most patients required a total daily dose between 1,500 mg and 3,000 mg to reduce plasma phosphate levels to less than 6.0 mg/dL. Doses were generally titrated in increments of 750 mg/day.

Information for FOSRENOL Chewable Tablets

Chew or crush FOSRENOL Chewable Tablets completely before swallowing. Do not swallow intact FOSRENOL Chewable Tablets.

Information for FOSRENOL Oral Powder

Sprinkle FOSRENOL Oral Powder on a small quantity of applesauce or other similar food and consume immediately. Do not open until ready to use. Do not store FOSRENOL Oral Powder for future use once mixed with food. Because FOSRENOL Oral Powder is insoluble, do not attempt to dissolve in liquid for administration.

Consider using the oral powder formulation in patients with poor dentition or who have difficulty chewing tablets.

3 DOSAGE FORMS AND STRENGTHS

- FOSRENOL Chewable Tablets: 500 mg, 750 mg, and 1,000 mg.
- FOSRENOL Oral Powder: 750 mg and 1,000 mg.

4 CONTRAINDICATIONS

Contraindicated in patients with:
- hypersensitivity to FOSRENOL or to any ingredient in the formulation.

- bowel obstruction, including ileus and fecal impaction.

5 WARNINGS AND PRECAUTIONS

5.1 Gastrointestinal Adverse Effects

Serious cases of gastrointestinal obstruction, ileus, subileus, gastrointestinal perforation, and fecal impaction have been reported in patients taking lanthanum, some requiring surgery or hospitalization. Consider discontinuing FOSRENOL in patients without another explanation for severe gastrointestinal symptoms.

Risk factors for gastrointestinal obstruction and gastrointestinal perforation identified from post-marketing reports in patients taking FOSRENOL Chewable Tablets include abnormal gastrointestinal anatomy (e.g., diverticular disease, peritonitis, history of gastrointestinal surgery, gastrointestinal cancer, gastrointestinal ulceration), hypomotility disorders (e.g., constipation, ileus, subileus, diabetic gastroparesis), and the use of medications known to potentiate these effects. Some cases were reported in patients with no history of gastrointestinal disease.

Patients with acute peptic ulcer, ulcerative colitis, Crohn's disease, or bowel obstruction were not included in FOSRENOL clinical studies [see Contraindications (4)].

Advise patients who are prescribed FOSRENOL Chewable Tablets to chew the tablet completely and not to swallow them whole. Serious gastrointestinal complications have been reported in association with unchewed or incompletely chewed tablets [see Adverse Reactions (6.2)].

5.2 Diagnostic Tests

FOSRENOL has radio-opaque properties and therefore may give the appearance typical of an imaging agent during abdominal X-ray procedures. Postmarketing reports of product residue have been reported during endoscopic imaging.

6 ADVERSE REACTIONS

The following adverse reactions are discussed in greater detail in other sections of the labeling:

- Gastrointestinal Adverse Effects [see Warnings and Precautions (5.1)]

6.1 Clinical Trials Experience

Because clinical trials are conducted under widely varying conditions, adverse reaction rates observed in the clinical trials of a drug cannot be directly compared to rates in the clinical trials of another drug and may not reflect the rates observed in practice.

Overall, the safety profile of FOSRENOL has been studied in over 5,200 subjects in completed clinical trials. The most common adverse reactions for FOSRENOL were gastrointestinal events, such as nausea, vomiting, and abdominal pain and they generally abated over time with continued dosing.

In double-blind, placebo-controlled studies where a total of 180 and 95 patients with ESRD were randomized to FOSRENOL chewable tablet and placebo, respectively, for 4 to 6 weeks of treatment, the most common reactions that were more frequent (≥5% difference) in the FOSRENOL group were nausea, vomiting, and abdominal pain (Table 1).

Table 1. Adverse Reactions [Expressed as the event rate for each term] That Were More Common on FOSRENOL in Placebo-Controlled, Double-Blind Studies with Treatment Periods of 4 to 6 Weeks
 | FOSRENOL % (N=180) | Placebo % (N=95)
Nausea | 11 | 5
Vomiting | 9 | 4
Abdominal pain | 5 | 0

In an open-label, long-term 2-year extension study in 93 patients who had transitioned from other studies, resulting in a total of up to 6 years treatment, mean baseline values and changes in transaminases were similar to those observed in the earlier comparative studies, with little change during treatment.

The safety of FOSRENOL was studied in two long-term, open-label clinical trials, which included 1,215 patients treated with FOSRENOL and 944 with alternative therapy. Fourteen percent (14%) of patients treated with FOSRENOL discontinued treatment due to adverse events. Gastrointestinal adverse reactions, such as nausea, diarrhea, and vomiting were the most common types of event leading to discontinuation.

In pooled active comparator controlled clinical trials, hypocalcemia was noted with an incidence of approximately 5% in both lanthanum and active comparator groups. A nonclinical study and a phase 1 study have shown reduced absorption of calcium in the intestine with lanthanum carbonate treatment.

In a crossover study in 72 healthy individuals comparing FOSRENOL Chewable Tablets to FOSRENOL Oral Powder, gastrointestinal adverse reactions such as nausea, diarrhea, and vomiting were more common for the oral powder formulation (18%) than for the chewable tablets (7%).

6.2 Postmarketing Experience

The following adverse reactions have been identified during post-approval use of FOSRENOL. Because these reactions are reported voluntarily from a population of uncertain size, it is not always possible to reliably estimate their frequency or establish a causal relationship to drug exposure.

Cases of constipation, intestinal perforation, intestinal obstruction, ileus, subileus, dyspepsia, allergic skin reactions, hypophosphatemia, and tooth injury while chewing the tablet have been reported.

7 DRUG INTERACTIONS

7.1 Drugs Binding to Antacids

There is a potential for FOSRENOL to interact with compounds which bind to cationic antacids (i.e., aluminum-, magnesium-, or calcium-based); therefore, do not administer such compounds within 2 hours of dosing with FOSRENOL. Examples of relevant classes of compounds where antacids have been demonstrated to reduce bioavailability include antibiotics (such as quinolones, ampicillin, and tetracyclines), thyroid hormones, ACE inhibitors, statin lipid regulators, and anti-malarials.

7.2 Quinolone Antibiotics

Co-administration of FOSRENOL with quinolone antibiotics may reduce the extent of their absorption. The bioavailability of oral ciprofloxacin was decreased by approximately 50% when taken with FOSRENOL in a single-dose study in healthy volunteers. Administer oral quinolone antibiotics at least 1 hour before or 4 hours after FOSRENOL. When oral quinolones are given for short courses, consider eliminating the doses of FOSRENOL that would normally be scheduled near the time of quinolone intake to improve quinolone absorption [see Clinical Pharmacology (12.3)].

7.3 Levothyroxine

The bioavailability of levothyroxine was decreased by approximately 40% when taken together with FOSRENOL. Administer thyroid hormone replacement therapy at least 2 hours before or 2 hours after dosing with FOSRENOL and monitor thyroid stimulating hormone (TSH) levels [see Clinical Pharmacology (12.3)].

7.4 Use with Other Oral Medications

There are no empirical data on avoiding drug interactions between FOSRENOL and most concomitant oral drugs. For oral medications where a reduction in the bioavailability of that medication would have a clinically significant effect on its safety or efficacy, consider separation of the timing of the administration of the two drugs. The duration of separation depends upon the absorption characteristics of the medication concomitantly administered, such as the time to reach peak systemic levels and whether the drug is an immediate-release or an extended-release product. Consider monitoring clinical responses or blood levels of concomitant medications that have a narrow therapeutic range.

8 USE IN SPECIFIC POPULATIONS

8.1 Pregnancy

Risk Summary

Available data from case reports with use of FOSRENOL in pregnant women are insufficient to identify a drug-associated risk of major birth defects, miscarriage, or adverse maternal or fetal outcomes. In animal reproduction studies, oral administration of lanthanum carbonate to pregnant rats and rabbits during organogenesis at doses 3 and 2.5 times, respectively, the maximum recommended human dose (MRHD), resulted in no adverse developmental effects. In rabbits, lanthanum carbonate doses 5 times the MRHD was associated with maternal toxicity and resulted in increased post-implantation loss, reduced fetal weights, and delayed fetal ossification (see Data). Deposition of lanthanum into developing bone, including growth plate, was observed in juvenile animals in long-term animal studies with lanthanum carbonate [see Use in Specific Populations (8.4)]. Use a non-lanthanum containing phosphate binder in a pregnant woman.

The estimated background risk of major birth defects and miscarriage for the indicated population is unknown. All pregnancies have a background risk of birth defect, loss, or other adverse outcomes. In the U.S. general population, the estimated background risk of major birth defect and miscarriage in clinically recognized pregnancies is 2% to 4% and 15% to 20%, respectively.

Data

Animal Data

In pregnant rats, oral administration of lanthanum carbonate at doses as high as 2,000 mg/kg/day during organogenesis resulted in no evidence of harm to the fetus. The MRHD for FOSRENOL is 5,725 mg, representing a dose of 95.4 mg/kg, or 3,530 mg/m^2 for a 60-kg patient. The 2,000-mg/kg/day dose in the rat is equivalent to 12,000 mg/m^2, 3 times the MRHD. In pregnant rabbits, oral administration of lanthanum carbonate at 1,500 mg/kg/day (18,000 mg/m^2; 5 times the daily MRHD) during organogenesis was associated with increased post-implantation loss, reduced fetal weights, and delayed fetal ossification. No effects on the pregnant rabbits or fetuses were observed at 750 mg/kg/day (9,000 mg/m^2; 2.5 times the MRHD).

In a pre- and postnatal development study in the rat, pregnant rats were dosed at up to 2,000 mg/kg/day (12,000 mg/m^2/day; equivalent to 3 times the MRHD) from day 6 of pregnancy through 20 days postpartum (including lactation). At 2,000 mg/kg/day, no maternal toxicity was observed, nor were any changes seen with respect to gestational length or delivery; however, piloerection/pallor, delayed eye opening, decreased body weight, and delayed sexual development were observed in the offspring at 2,000 mg/kg/day. At 200 and 600 mg/kg/day (equivalent to 0.3 and 1 time the MRHD, respectively), slight delays in sexual development (delayed vaginal opening) were observed in the female offspring [see Nonclinical Toxicology (13.2)].

8.2 Lactation

Risk Summary

There are no data on the presence of lanthanum carbonate from FOSRENOL in human milk, the effects on the breastfed infant, or the effects on milk production. Deposition of lanthanum into developing bone, including growth plate, was observed in juvenile animals in long-term animal studies with lanthanum carbonate [see Use in Specific Populations (8.4)]. Use a non-lanthanum containing phosphate binder in a lactating woman.

8.4 Pediatric Use

The safety and efficacy of FOSRENOL in pediatric patients have not been established. While growth abnormalities were not identified in long-term animal studies, lanthanum was deposited into developing bone, including growth plate. The consequences of such deposition in developing bone in pediatric patients are unknown; therefore, the use of FOSRENOL in this population is not recommended.

8.5 Geriatric Use

Of the total number of patients in clinical studies of FOSRENOL, 32% (538) were ≥65 years of age, while 9.3% (159) were ≥75 years of age. No overall differences in safety or effectiveness were observed between patients ≥65 years of age and younger patients.

10 OVERDOSAGE

The symptoms associated with overdose are adverse reactions such as headache, nausea and vomiting. In clinical trials in healthy adults, gastrointestinal (GI) symptoms were reported with daily doses up to 6,000 mg/day of lanthanum carbonate administered with food. Given the topical activity of lanthanum in the gut, and the excretion of the majority of the dose in feces, supportive therapy is recommended for overdosage. Lanthanum carbonate was not acutely toxic in animals by the oral route. No deaths and no adverse effects occurred in mice, rats, or dogs after single oral doses of 2,000 mg/kg (1.7, 3.4, and 11.3 times the MRHD, respectively, on a mg/m^2 basis).

11 DESCRIPTION

FOSRENOL contains lanthanum carbonate with molecular formula La2(CO3)3 xH2O (on average x=4-5 moles of water) and molecular weight 457.8 (anhydrous mass). Lanthanum carbonate is described as white to almost-white powder. Lanthanum carbonate is practically insoluble in water and is insoluble in organic solvents; it dissolves in dilute mineral acids with effervescence.

Each FOSRENOL, white to off-white, chewable tablet contains lanthanum carbonate hydrate equivalent to 500, 750, or 1,000 mg of elemental lanthanum and the following inactive ingredients: colloidal silicon dioxide, dextrates (hydrated), magnesium stearate.

FOSRENOL Oral Powder is a white to off-white powder containing lanthanum carbonate hydrate equivalent to 750 or 1,000 mg of elemental lanthanum and the following inactive ingredients: colloidal silicon dioxide, dextrates (hydrated), magnesium stearate.

12 CLINICAL PHARMACOLOGY

12.1 Mechanism of Action

FOSRENOL is a phosphate binder that reduces absorption of phosphate by forming insoluble lanthanum phosphate complexes that pass through the GI tract unabsorbed. Both serum phosphate and calcium phosphate product are reduced as a consequence of the reduced dietary phosphate absorption.

12.2 Pharmacodynamics

In vitro studies have shown that lanthanum binds phosphate in the physiologically relevant pH range of 3 to 7. In simulated gastric fluid, lanthanum binds approximately 97% of the available phosphate at pH 3-5 and 67% at pH 7, when lanthanum is present in a two-fold molar excess to phosphate. Bile acids have not been shown to affect the phosphate binding affinity of lanthanum. In order to bind dietary phosphate, FOSRENOL must be administered with or immediately after meals.

In five phase 1 pharmacodynamic studies comparing the reduction from baseline of urinary phosphorus excretion in healthy volunteers (N=143 taking lanthanum carbonate), it was shown that the mean intestinal phosphate binding capacity of lanthanum ranged from 235 to 468 mg phosphorus/day when lanthanum was administered at a dose of 3 g per day with food. By comparison, in one study with an untreated control group (n=10) and another study with a placebo group (n=3), the corresponding mean changes from baseline were 3 mg phosphorus/day and 87 mg phosphorus/day, respectively.

In healthy subjects, FOSRENOL Oral Powder and FOSRENOL Chewable Tablets produce similar effects on urinary phosphate excretion.

12.3 Pharmacokinetics

Absorption and Distribution - Following single- or multiple-dose oral administration of FOSRENOL to healthy subjects, the concentration of lanthanum in plasma was very low (bioavailability <0.002%). Following oral administration in patients, the mean lanthanum Cmax was 1.0 ng/mL. During long-term administration (52 weeks) in patients with ESRD, the mean lanthanum concentration in plasma was approximately 0.6 ng/mL. There was a minimal increase in plasma lanthanum concentrations with increasing doses within the therapeutic dose range. The timing of food intake relative to lanthanum administration (during and 30 minutes after food intake) has a negligible effect on the systemic level of lanthanum.

Systemic exposure to lanthanum was approximately 30% higher following administration of FOSRENOL Oral Powder when compared to FOSRENOL Chewable Tablets. However, systemic exposure to lanthanum from both formulations in this study was within the range seen in previous pharmacokinetic studies of Chewable Tablets in healthy individuals.

In vitro, lanthanum is highly bound (>99%) to human plasma proteins, including human serum albumin, α1-acid glycoprotein, and transferrin. Binding to erythrocytes in vivo is negligible in rats.

In animal studies, lanthanum concentrations in several tissues, particularly gastrointestinal tract, mesenteric lymph nodes, bone, and liver, increased over time to levels several orders of magnitude higher than those in plasma. The level of lanthanum in the liver was higher in renally impaired rats due to higher intestinal absorption. Lanthanum was found in the lysosomes and the biliary canal consistent with transcellular transport. Steady state tissue concentrations in bone and liver were achieved in dogs between 4 and 26 weeks. Relatively high levels of lanthanum remained in these tissues for longer than 6 months after cessation of dosing in dogs. There is no evidence from animal studies that lanthanum crosses the blood-brain barrier.

In 105 bone biopsies from patients treated with FOSRENOL for up to 4.5 years, rising levels of lanthanum were noted over time. Estimates of elimination half-life from bone ranged from 2.0 to 3.6 years. Steady state bone concentrations were not reached during the period studied.

Metabolism and Elimination - Lanthanum is not metabolized. Lanthanum was cleared from plasma of patients undergoing dialysis with an elimination half-life of 53 hours following discontinuation of therapy.

No information is available regarding the mass balance of lanthanum in humans after oral administration. In rats and dogs, the mean recovery of lanthanum after an oral dose was about 99% and 94%, respectively, and was essentially all from feces. Biliary excretion is the predominant route of elimination for circulating lanthanum in rats. In healthy volunteers administered intravenous (IV) lanthanum as the soluble chloride salt (120 mcg), renal clearance was less than 2% of total plasma clearance.

Drug Interactions

FOSRENOL has a low potential for systemic drug-drug interactions because of the very low bioavailability of lanthanum and because it is not a substrate or inhibitor of major cytochrome P450 enzyme groups involved in drug metabolism (CYP1A2, CYP2C9/10, CYP2C19, CYP2D6, and CYP3A4/5).

FOSRENOL does not alter gastric pH; therefore, FOSRENOL drug interactions based on altered gastric pH are not expected.

In an in vitro investigation, lanthanum did not form insoluble complexes when mixed in simulated gastric fluid with warfarin, digoxin, furosemide, phenytoin, metoprolol, and enalapril. Clinical studies have shown that FOSRENOL (three doses of 1,000 mg on the day prior to exposure and one dose of 1,000 mg on the day of co-administration) administered 30 minutes earlier did not alter the pharmacokinetics of oral warfarin (10 mg), digoxin (0.5 mg), or metoprolol (100 mg). Potential pharmacodynamic interactions between lanthanum and these drugs (e.g., bleeding time or prothrombin time) were not evaluated. None of the drug interaction studies were done with the maximum recommended therapeutic dose of lanthanum carbonate. No drug interaction studies assessed the effects of drugs on phosphate binding by lanthanum carbonate.

Ciprofloxacin

In a randomized, two–way crossover study in healthy volunteers examining the interaction potential of a single oral dose of ciprofloxacin (750 mg) alone and with lanthanum carbonate (1 g three times a day), the maximum plasma concentration of ciprofloxacin was reduced by 56% and the area under the ciprofloxacin plasma concentration-time curve was reduced by 54%. The 24-hour urinary recovery of ciprofloxacin was reduced 52% by FOSRENOL [see Drug Interactions (7.2)].

Levothyroxine

In a single-dose crossover study of levothyroxine (1 mg) with or without simultaneous administration of a single dose of FOSRENOL (500 mg) in six euthyroid normal healthy volunteers, the area under the serum T4 concentration-time curve was decreased by 40% [see Drug Interactions (7.3)].

Fat-Soluble Vitamins

FOSRENOL appears not to affect the availability of fat-soluble vitamins (A, D, E, and K) or other nutrients [see Clinical Studies (14.2)].

Citrate

Citrate did not increase the absorption of lanthanum.

13 NONCLINICAL TOXICOLOGY

13.1 Carcinogenesis, Mutagenesis, Impairment of Fertility

Oral administration of lanthanum carbonate to rats for up to 104 weeks, at doses up to 1,500 mg of the salt per kg/day (2.5 times the MRHD of 5,725 mg, on a mg/m^2 basis, assuming a 60-kg patient) revealed no evidence of carcinogenic potential. In the mouse, oral administration of lanthanum carbonate for up to 99 weeks, at a dose of 1,500 mg/kg/day (1.3 times the MRHD) was associated with an increased incidence of glandular stomach adenomas in male mice.

Lanthanum carbonate tested negative for mutagenic activity in an in vitro Ames assay using Salmonella typhimurium and Escherichia coli strains and in vitro HGPRT gene mutation and chromosomal aberration assays in Chinese hamster ovary cells. Lanthanum carbonate also tested negative in an oral mouse micronucleus assay at doses up to 2,000 mg/kg (1.7 times the MRHD), and in micronucleus and unscheduled DNA synthesis assays in rats given IV lanthanum chloride at doses up to 0.1 mg/kg, a dose that produced plasma lanthanum concentrations greater than 2,000 times the peak human plasma concentration.

Lanthanum carbonate, at doses up to 2,000 mg/kg/day (3.4 times the MRHD), did not affect fertility or mating performance of male or female rats.

13.2 Animal Toxicology and/or Pharmacology

In pregnant rats, oral administration of lanthanum carbonate at doses as high as 2,000 mg/kg/day (3.4 times the MRHD) resulted in no evidence of harm to the fetus. In pregnant rabbits, oral administration of lanthanum carbonate at 1,500 mg/kg/day (5 times the MRHD) was associated with a reduction in maternal body weight gain and food consumption, increased post-implantation loss, reduced fetal weights, and delayed fetal ossification. No effects on pregnant rabbits or fetuses were observed at 750 mg/kg/day (2.5 times the MRHD). Lanthanum carbonate administered to rats from implantation through lactation at 2,000 mg/kg/day (3.4 times the MRHD) caused delayed eye opening, reduction in body weight gain, and delayed sexual development (preputial separation and vaginal opening) of the offspring. At 200 and 600 mg/kg/day (equivalent to 0.3 and 1 time the MRHD, respectively), slight delays in vaginal opening were observed in the female offspring.

14 CLINICAL STUDIES

The effectiveness of FOSRENOL in reducing serum phosphorus in patients with ESRD was demonstrated in one short-term, placebo-controlled, double-blind dose-ranging study; two placebo-controlled, randomized withdrawal studies; and two long-term, active-controlled, open-label studies in patients undergoing either hemodialysis or peritoneal dialysis.

14.1 Double-Blind Placebo-Controlled Studies

One-hundred and forty-four patients with chronic renal failure undergoing hemodialysis and with elevated phosphate levels were randomized to double-blind treatment at a fixed dose of lanthanum carbonate of 225 mg (n=27), 675 mg (n=29), 1,350 mg (n=30), or 2,250 mg (n=26) or placebo (n=32) in divided doses with meals. Fifty-five percent of subjects were male, 71% black, 25% white, and 4% of other races. The mean age was 56 years and the duration of dialysis ranged from 0.5 to 15.3 years. Steady-state effects were achieved after two weeks. The effect after six weeks of treatment is shown in Figure 1.

Figure 1. Difference in Phosphate Reduction in the FOSRENOL and Placebo Group in a 6-Week, Dose-Ranging, Double-Blind Study in Patients with ESRD (with 95% Confidence Intervals)

One-hundred and eighty-five patients with ESRD undergoing either hemodialysis (n=146) or peritoneal dialysis (n=39) were enrolled in two placebo-controlled, randomized withdrawal studies. Sixty-four percent of subjects were male, 28% black, 62% white, and 10% of other races. The mean age was 58.4 years and the duration of dialysis ranged from 0.2 to 21.4 years. After titration of lanthanum carbonate to achieve a phosphate level between 4.0 and 5.6 mg/dL in one study (doses up to 2,250 mg/day) or ≤5.9 mg/dL in the second study (doses up to 3,000 mg/day) and maintenance through 6 weeks, patients were randomized to lanthanum or placebo. During the placebo-controlled, randomized withdrawal phase (four weeks), the phosphorus concentration rose in the placebo group by 1.7 mg/dL in one study and 1.9 mg/dL in the other study relative to patients who remained on lanthanum carbonate therapy.

14.2 Open-Label Active-Controlled Studies

Two long-term open-label studies were conducted, involving a total of 2,028 patients with ESRD undergoing hemodialysis. Patients were randomized to receive FOSRENOL or alternative phosphate binders for up to six months in one study and two years in the other. The daily FOSRENOL doses, divided and taken with meals, ranged from 375 mg to 3,000 mg. Doses were titrated to reduce serum phosphate levels to a target level. The daily doses of the alternative therapy were based on current prescribing information or those commonly utilized. Both treatment groups had similar reductions in serum phosphate of about 1.8 mg/dL. Maintenance of reduction was observed for up to three years in patients treated with FOSRENOL in long-term, open-label extensions.

No effects of FOSRENOL on serum levels of 25-dihydroxy vitamin D3, vitamin A, vitamin B12, vitamin E, and vitamin K were observed in patients who were monitored for 6 months.

Paired bone biopsies (at baseline and at one or two years) in 69 patients randomized to either FOSRENOL or calcium carbonate in one study and 99 patients randomized to either FOSRENOL or alternative therapy in a second study showed no differences in the development of mineralization defects between the groups.

Vital status was known for over 2,000 patients, 97% of those participating in the clinical program during and after receiving treatment. The adjusted yearly mortality rate (rate/years of observation) for patients treated with FOSRENOL or alternative therapy was 6.6%.

16 HOW SUPPLIED/STORAGE AND HANDLING

16.1 FOSRENOL Chewable Tablets

FOSRENOL is supplied as a chewable tablet in three dosage strengths for oral administration: 500-mg tablets, 750-mg tablets, and 1,000-mg tablets. Each chewable tablet is white to off-white round, flat with a beveled edge, and debossed on one side with 'S405' above the dosage strength corresponding to the content of elemental lanthanum.

500-mg Patient Pack (2 bottles of 45 tablets, NDC 54092-252-45, per each patient pack) NDC 54092-252-90.

750-mg Patient Pack (6 bottles of 15 tablets, NDC 54092-253-15, per each patient pack) NDC 54092-253-90.

1,000-mg Patient Pack (9 bottles of 10 tablets, NDC 54092-254-10, per each patient pack) NDC 54092-254-90.

16.2 FOSRENOL Oral Powder

FOSRENOL Oral Powder is supplied in two dosage strengths for oral administration: 750 mg and 1,000 mg. Each 750-mg and 1,000-mg stick pack contains 2.1 g and 2.8 g oral powder, respectively, packed in a polyethylene terephthalate/aluminum/polyethylene laminate.

Strength | Carton of 10 Stick Packs | Patient Pack of 9 Cartons
750 mg | NDC 54092-256-01 | NDC 54092-256-02
1,000 mg | NDC 54092-257-01 | NDC 54092-257-02

Storage and Handling

Store FOSRENOL Chewable Tablets and FOSRENOL Oral Powder at 25°C (77°F): excursions permitted to 15°C to 30°C (59°F to 86°F).
[See USP controlled room temperature.]

17 PATIENT COUNSELING INFORMATION

- Advise the patient to read the FDA-approved patient labeling (Medication Guide).
- Advise patients to take FOSRENOL with or immediately after meals [see Dosage and Administration (2)].
- Instruct patients on concomitant medications that should be dosed apart from FOSRENOL [see Drug Interactions (7)].
- Instruct patients who are prescribed FOSRENOL Chewable Tablets to chew or crush tablets completely before swallowing. Emphasize that FOSRENOL Chewable Tablets should not be swallowed intact. Consider crushing FOSRENOL Chewable Tablets completely or prescribing the oral powder formulation for patients with poor dentition or who have difficulty chewing tablets [see Dosage and Administration (2)].
- Instruct patients who are prescribed FOSRENOL Oral Powder to sprinkle powder on a small quantity of applesauce or other similar food. Patients should be instructed to consume the entire dose immediately. FOSRENOL Oral Powder is insoluble, so do not attempt to dissolve the powder in liquid for administration [see Dosage and Administration (2)].
- Advise patients who are taking an oral medication where a reduction in the bioavailability of that medication would have a clinically significant effect on its safety or efficacy to separate the dosing of FOSRENOL from the dosing of the affected drug by several hours [see Drug Interactions (7)].
- Advise patients to notify their physician that they are taking FOSRENOL prior to an abdominal X-ray or if they have a history of gastrointestinal disease [see Warnings and Precautions (5.1, 5.2)].

FOSRENOL Chewable Tablets manufactured by Patheon Manufacturing Services LLC,
5900 Martin Luther King Jr. Highway
Greenville, NC 27834

FOSRENOL Oral Powder manufactured by Catalent Germany Schorndorf GmbH,
Steinbeisstrasse 1-2
D-73614 Schorndorf
Germany

Distributed by:
Takeda Pharmaceuticals America, Inc.
Cambridge, MA 02142

FOSRENOL and are registered trademarks of Takeda Pharmaceuticals U.S.A., Inc.
© 2024 Takeda Pharmaceuticals U.S.A., Inc. All rights reserved.

Patented: see www.takeda.com/en-us/patents

MEDICATION GUIDE FOSRENOL® (foss-wren-all) (lanthanum carbonate)

Read this Medication Guide before you start taking FOSRENOL and each time you get a refill. There may be new information. This information does not take the place of talking to your healthcare provider about your medical condition or treatment.

What is the most important information I should know about FOSRENOL?

FOSRENOL may cause a bowel blockage, a hole in the bowel, or severe constipation, which can be serious, and sometimes lead to surgery or treatment in a hospital.

- You may have a higher risk of bowel blockage, a hole in the bowel, or severe constipation if you take FOSRENOL and have:
  - a history of surgery, ulcers or cancer in the stomach or bowel
  - a history of bowel blockage, or problems resulting in a decreased movement of food through your stomach and bowel (e.g., feeling full quickly after eating or constipation)
  - an infection or inflammation of the stomach/bowel (peritonitis)

Do not swallow FOSRENOL Chewable Tablets whole. Chew tablets completely before swallowing. If you cannot chew tablets completely, you may crush the tablets thoroughly before swallowing or discuss the oral powder formulation with your healthcare provider.

What is FOSRENOL?

FOSRENOL is a prescription medicine used in people with end-stage renal disease (ESRD) to lower the amount of phosphate in the blood.

Who should not take FOSRENOL?

Do not take FOSRENOL if you:

- are allergic to lanthanum carbonate or any of the other ingredients of this medicine
- have blocked bowels
- have severe constipation

FOSRENOL has not been studied in children and adolescents under 18 years of age.

What should I tell my healthcare provider before taking FOSRENOL?

FOSRENOL may not be right for you. Before starting FOSRENOL, tell your healthcare provider if you:

- have a history of surgery, ulcers or cancer in the stomach or bowel
- have a history of a bowel blockage, constipation, or problems resulting in a decreased movement of food through your stomach and bowel especially if you also have diabetes
- have ulcerative colitis, Crohn's disease or an infection or inflammation of the stomach/bowel (peritonitis)
- plan to have an X-ray of your stomach (abdomen)
- have any other medical conditions
- are pregnant, plan to become pregnant, or plan to breastfeed. Tell your healthcare provider about all the medicines you take, including prescription and non-prescription medicines, vitamins, and herbal supplements.

Especially tell your healthcare provider if you take:

- antacids
- antibiotics
- thyroid medicine

Know the medicines you take. Keep a list of them and show it to your healthcare provider and pharmacist when you get a new medicine.

How should I take FOSRENOL?

- Take FOSRENOL exactly as prescribed by your healthcare provider
- Your healthcare provider will tell you how much FOSRENOL to take
- Your healthcare provider may change your dose if needed
- Chewable Tablets – Do not swallow tablets whole. Chew tablets completely before swallowing. If you cannot chew tablets completely, or if you have tooth disease, you may crush the tablets thoroughly before swallowing or discuss the oral powder formulation with your healthcare provider.
- Oral Powder – Sprinkle powder on a small quantity of applesauce or other similar food. Consume the entire dose immediately. FOSRENOL Oral Powder will not dissolve in liquid.
- Take FOSRENOL with or right after meals
- If you take an antacid medicine, take the antacid 2 hours before or 2 hours after you take FOSRENOL
- If you take medicine for your thyroid (levothyroxine), take the thyroid medicine 2 hours before or 2 hours after you take FOSRENOL
- If you take an antibiotic medicine, take the antibiotic 1 hour before or 4 hours after you take FOSRENOL

What are possible or reasonably likely side effects of FOSRENOL?

See "What is the most important information I should know about FOSRENOL?"

The most common side effects of FOSRENOL include:

- nausea
- vomiting
- diarrhea
- stomach pain

Tell your healthcare provider if you have any side effect that bothers you or that does not go away.

These are not all the side effects of FOSRENOL. For more information, ask your healthcare provider or pharmacist.

Call your doctor for medical advice about side effects. You may report side effects to FDA at 1-800-FDA-1088.

How should I store FOSRENOL?

- Store FOSRENOL between 59°F to 86°F (15°C to 30°C).

Keep FOSRENOL and all medicines out of the reach of children.

General information about FOSRENOL

Medicines are sometimes prescribed for purposes other than those listed in a Medication Guide. Do not use FOSRENOL for a condition for which it was not prescribed. Do not give FOSRENOL to other people, even if they have the same condition. It may harm them.

This Medication Guide summarizes the most important information about FOSRENOL. If you would like more information, talk with your healthcare provider. You can ask your pharmacist or healthcare provider for information about FOSRENOL that is written for healthcare professionals.

For more information go to www.FOSRENOL.com or call 1-877-825-3327.

What are the ingredients in FOSRENOL?

Active ingredient: lanthanum carbonate

Inactive ingredients: colloidal silicon dioxide NF, dextrates (hydrated) NF, and magnesium stearate NF.

Distributed by:
Takeda Pharmaceuticals America, Inc.
Cambridge, MA 02142

FOSRENOL and are registered trademarks of Takeda Pharmaceuticals U.S.A., Inc.
© 2024 Takeda Pharmaceuticals U.S.A., Inc. All rights reserved.

This Medication Guide has been approved by the US Food and Drug Administration.

Issued [12/2024]

PRINCIPAL DISPLAY PANEL - 500 mg Tablet Bottle Label

NDC 54092-252-45

FOSRENOL®
(lanthanum carbonate)
chewable tablets

500 mg

Do not swallow tablets whole.
Chew or crush tablets completely
before swallowing.
Take with or immediately after meals.

ATTENTION PHARMACIST: Each patient is required
to receive the enclosed Medication Guide.

45 TABLETS
Rx only
Takeda

PRINCIPAL DISPLAY PANEL - 500 mg Tablet Bottle Package

NDC 54092-252-90

FOSRENOL®
(lanthanum carbonate)
chewable tablets

500 mg

Do not swallow tablets whole.
Chew or crush tablets completely
before swallowing.
Take with or immediately after
meals.

2 bottles/45 chewable tablets each

Rx only

Active Ingredient: Each
tablet contains 500 mg
of lanthanum as lanthanum
carbonate hydrate

Inactive Ingredients:
Colloidal silicon dioxide,
dextrates, and magnesium
stearate.

See package insert for full
prescribing information.
Store at 25°C (77°F)
excursions permitted to
15-30°C (59-86°F)
[see USP Controlled Room
Temperature]

Takeda

PRINCIPAL DISPLAY PANEL - 750 mg Tablet Bottle Label

NDC 54092-253-15

FOSRENOL®
(lanthanum carbonate)
chewable tablets

750 mg

Do not swallow tablets whole.
Chew or crush tablets completely
before swallowing.
Take with or immediately after meals.

ATTENTION PHARMACIST: Each patient is required
to receive the enclosed Medication Guide.

15 TABLETS
Rx only
Takeda

PRINCIPAL DISPLAY PANEL - 750 mg Tablet Bottle Package

NDC 54092-253-90

FOSRENOL®
(lanthanum carbonate)
chewable tablets

750 mg

Do not swallow tablets whole.
Chew or crush tablets completely
before swallowing.
Take with or immediately after meals.

6 bottles/15 chewable tablets each

Rx only

Active Ingredient: Each
tablet contains 750 mg
of lanthanum as lanthanum
carbonate hydrate

Inactive Ingredients:
Colloidal silicon dioxide,
dextrates, and magnesium
stearate.

See package insert for full
prescribing information.
Store at 25°C (77°F)
excursions permitted to
15-30°C (59-86°F)
[see USP Controlled Room
Temperature]

Takeda

PRINCIPAL DISPLAY PANEL - 1000 mg Tablet Bottle Label

NDC 54092-254-10

FOSRENOL®
(lanthanum carbonate)
chewable tablets

1000 mg

Do not swallow tablets whole.
Chew or crush tablets completely
before swallowing.
Take with or immediately after meals.

ATTENTION PHARMACIST: Each patient is required
to receive the enclosed Medication Guide.

10 TABLETS
Rx only
Takeda

PRINCIPAL DISPLAY PANEL - 1000 mg Tablet Bottle Package

NDC 54092-254-90

FOSRENOL®
(lanthanum carbonate)
chewable tablets

1000 mg

Do not swallow tablets whole.
Chew or crush tablets completely
before swallowing.
Take with or immediately after meals.

9 bottles/10 chewable tablets each

Rx only

Active Ingredient: Each
tablet contains 1000 mg
of lanthanum as lanthanum
carbonate hydrate

Inactive Ingredients:
Colloidal silicon dioxide,
dextrates, and magnesium
stearate.

See package insert for full
prescribing information.
Store at 25° C (77°F)
excursions permitted to
15-30°C (59-86°F)
[see USP Controlled Room
Temperature]

Takeda

PRINCIPAL DISPLAY PANEL - 750 mg Packet Carton - 10 Stick Pack

NDC 54092-256-01

Fosrenol®
(lanthanum carbonate)
oral powder

750 mg

Mix with small quantity of soft food
and take immediately

Takeda

10 stick packs

Rx only

PRINCIPAL DISPLAY PANEL - 750 mg Packet Carton - 90 Stick Pack

NDC 54092-256-02

Fosrenol®
(lanthanum carbonate)
oral powder

750 mg

Mix with small quantity of soft food
and take immediately

Takeda

9 cartons, each carton contains 10 stick packs

Rx only

PRINCIPAL DISPLAY PANEL - 1000 mg Packet Carton - 10 Stick Pack

NDC 54092-257-01

Fosrenol®
(lanthanum carbonate)
oral powder

1000 mg

Mix with small quantity of soft food
and take immediately

Takeda

10 stick packs

Rx only

PRINCIPAL DISPLAY PANEL - 1000 mg Packet Carton - 90 Stick Pack

NDC 54092-257-02

Fosrenol®
(lanthanum carbonate)
oral powder

1000 mg

Mix with small quantity of soft food
and take immediately

Takeda

9 cartons, each carton contains 10 stick packs

Rx only